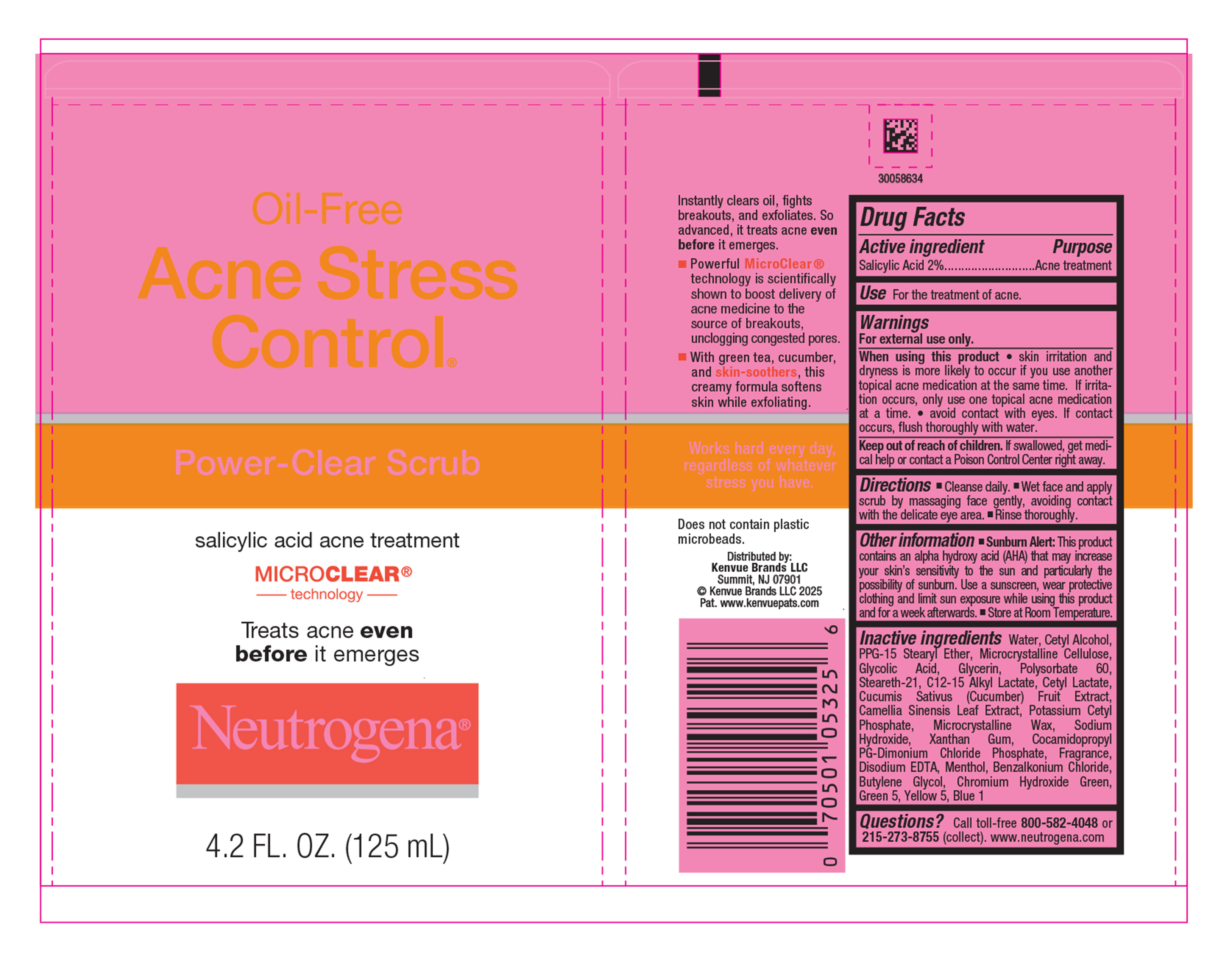 DRUG LABEL: Neutrogena Oil-Free Acne Stress Control Power Clear Scrub
NDC: 69968-0909 | Form: LIQUID
Manufacturer: Kenvue Brands LLC
Category: otc | Type: HUMAN OTC DRUG LABEL
Date: 20250820

ACTIVE INGREDIENTS: SALICYLIC ACID 20 mg/1 mL
INACTIVE INGREDIENTS: GLYCERIN; POLYSORBATE 60; STEARETH-21; POTASSIUM CETYL PHOSPHATE; COCAMIDOPROPYL PG-DIMONIUM CHLORIDE PHOSPHATE; YELLOW 5; MICROCRYSTALLINE CELLULOSE; GLYCOLIC ACID; C12-15 ALKYL LACTATE; MICROCRYSTALLINE WAX; CAMELLIA SINENSIS LEAF; XANTHAN GUM; BENZALKONIUM CHLORIDE; WATER; EDETATE DISODIUM; MENTHOL; CHROMIUM HYDROXIDE GREEN; BLUE 1; CETYL ALCOHOL; PPG-15 STEARYL ETHER; CETYL LACTATE; CUCUMIS SATIVUS (CUCUMBER) FRUIT; SODIUM HYDROXIDE; BUTYLENE GLYCOL; GREEN 5

Neutrogena® Oil-Free Acne Stress Control® Power Clear Scrub

Drug Facts

Active ingredient

Salicylic Acid 2%

Purpose

Acne treatment

Use

For the treatment of acne.

Warnings

For external use only.

- When using this product
- skin irritation and dryness is more likely to occur if you use another topical acne medication at the same time. If irritation occurs, only use one topical acne medication at a time.
- avoid contact with eyes. If contact occurs, flush thoroughly with water.

Keep out of reach of children. If swallowed, get medical help or contact a Poison Control Center right away.

Directions

- Cleanse daily.
- Wet face and apply scrub by massaging face gently, avoiding contact with the delicate eye area.
- Rinse thoroughly.

Other information

• Sunburn Alert: This product contains an alpha hydroxy acid (AHA) that may increase your skin’s sensitivity to the sun and particularly the possibility of sunburn. Use a sunscreen, wear protective clothing and limit sun exposure while using this product and for a week afterwards. • Store at Room Temperature.

Inactive ingredients

Water, Cetyl Alcohol, PPG-15 Stearyl Ether, Microcrystalline Cellulose, Glycolic Acid, Glycerin, Polysorbate 60, Steareth-21, C12-15 Alkyl Lactate, Cetyl Lactate, Cucumis Sativus (Cucumber) Fruit Extract, Camellia Sinensis Leaf Extract, Potassium Cetyl Phosphate, Microcrystalline Wax, Sodium Hydroxide, Xanthan Gum, Cocamidopropyl PG-Dimonium Chloride Phosphate, Fragrance, Disodium EDTA, Menthol, Benzalkonium Chloride, Butylene Glycol, Chromium Hydroxide Green, Green 5, Yellow 5, Blue 1

Questions?

Call toll-free 800-582-4048 or 215-273-8755 (collect). www.neutrogena.com

Distributed by:
Kenvue Brands LLC
Skillman, NJ 07901

PRINCIPAL DISPLAY PANEL - 125 mL Tube Label

Oil - Free

Acne Stress

Control®

Power-Clear Scrub

salicylic acid acne treatment

MICRO CLEAR®

technology

Treats acne even

before it emerges

Neutrogena®

4.2 FL. OZ. (125 mL)